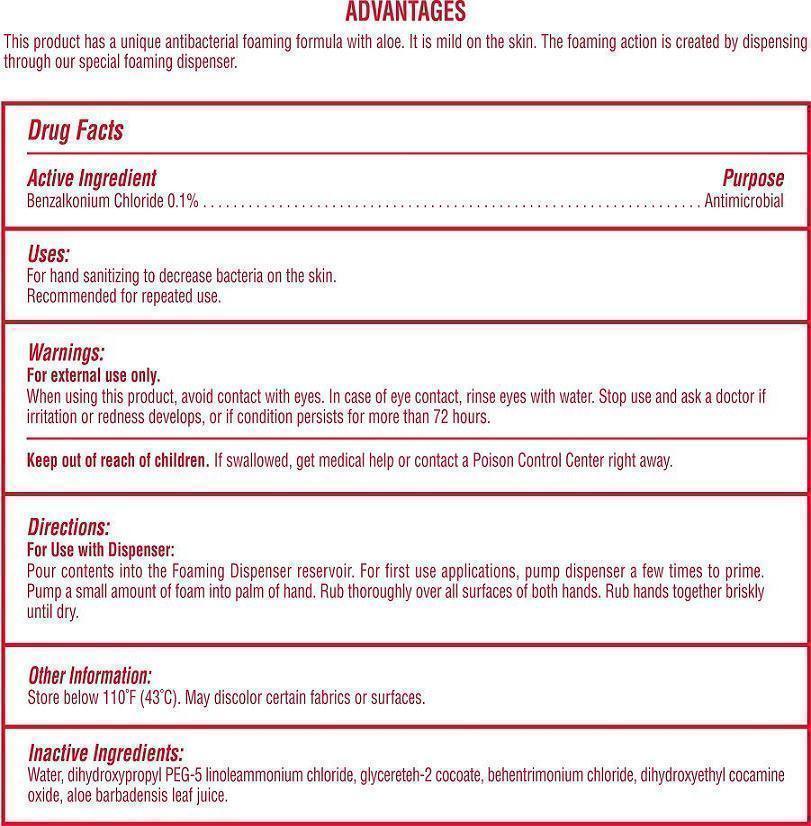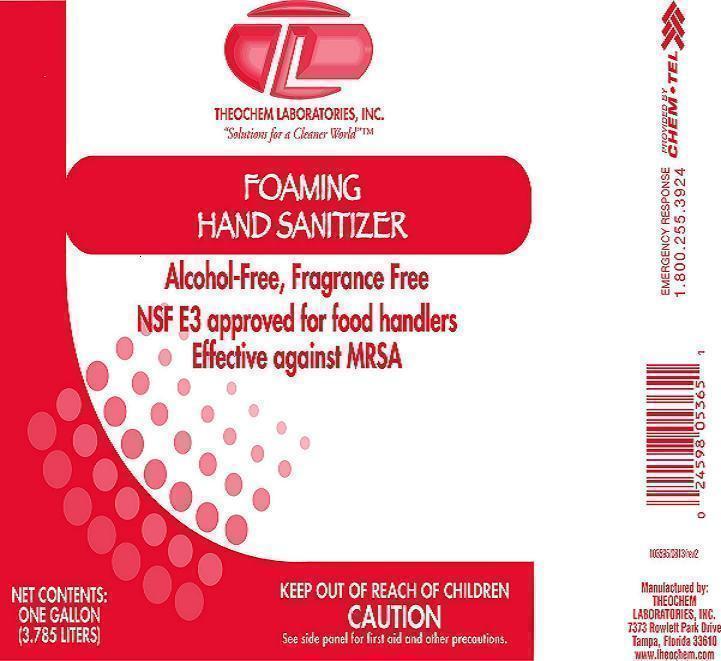 DRUG LABEL: Foaming Hand Sanitizer
NDC: 68878-119 | Form: LIQUID
Manufacturer: Theochem Laboratories Inc
Category: otc | Type: HUMAN OTC DRUG LABEL
Date: 20131213

ACTIVE INGREDIENTS: BENZALKONIUM CHLORIDE 0.1 mg/1 mL
INACTIVE INGREDIENTS: WATER

Foaming Hand Santizer

Active Ingredient

Benzalkonium Chloride 0.1%

Purpose

Antimicrobial

Uses

For hand sanitizing to decrease bacteria on the skin.
Recommended for repeated use.

Warnings

For external use only.
When using this product, avoid contact with eyes. In case of eye contact, flush eyes with water.
Stop use and ask a doctor if irritation or redness develops, or if condition persists for more than 72 hours.

Keep out of reach of children

If swallowed, get medical help or contact a Poison Control Center right away.

Directions:

Pour contents into the Foaming Dispenser reservoir. For first use applications, pump dispenser a few time to prime. Pump a small amount of foam into palm of hand. Rub thoroughly over all surfaces of both hands. Rub hands together briskly until dry.

Other Information

Store below 110 °F (43 °C). May discolor certain fabrics or surfaces.

Inactive Ingredients

Water, dihydroxypropyl PEG-5 linoleammonium chloride, glycereteh-2 cocoate, behentrimonium chloride, dihydroxyethyl cocamine oxide, aloe barbadensis leaf juice.